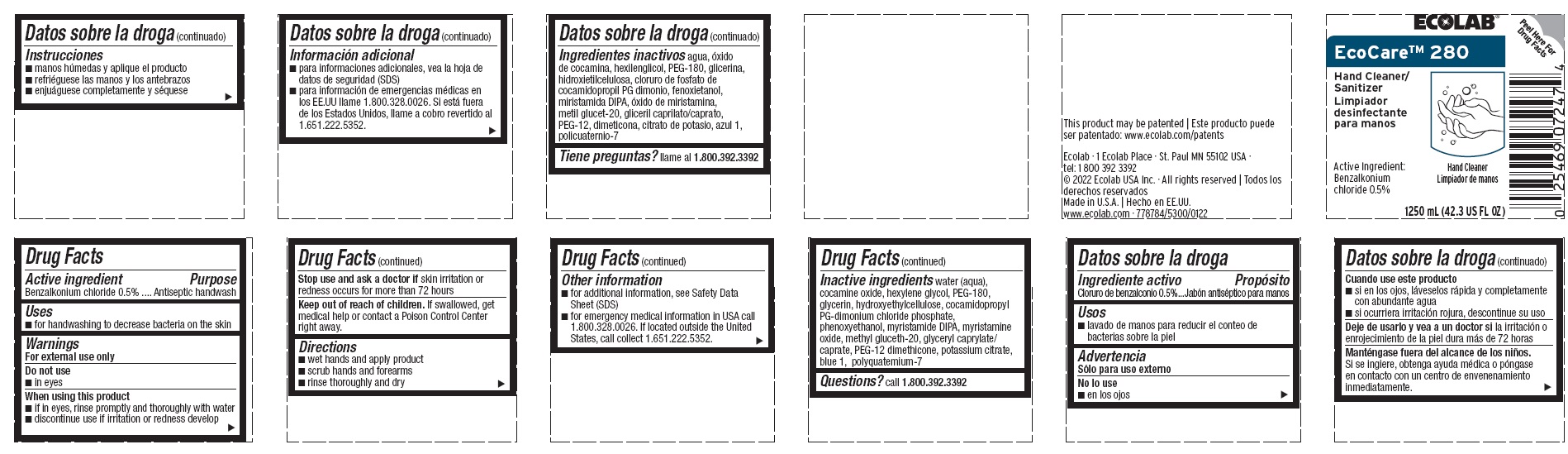 DRUG LABEL: EcoCare 280
NDC: 47593-646 | Form: SOLUTION
Manufacturer: Ecolab Inc.
Category: otc | Type: HUMAN OTC DRUG LABEL
Date: 20240806

ACTIVE INGREDIENTS: BENZALKONIUM CHLORIDE 5 mg/1 mL
INACTIVE INGREDIENTS: WATER; COCAMINE OXIDE; HEXYLENE GLYCOL; POLYETHYLENE GLYCOL 8000; GLYCERIN; HYDROXYETHYL CELLULOSE (4000 MPA.S AT 1%); COCAMIDOPROPYL PG-DIMONIUM CHLORIDE PHOSPHATE; PHENOXYETHANOL; MYRISTIC DIISOPROPANOLAMIDE; MYRISTAMINE OXIDE; METHYL GLUCETH-20; GLYCERYL MONO- AND DICAPRYLOCAPRATE; PEG-12 DIMETHICONE; POTASSIUM CITRATE; POLYQUATERNIUM-7 (70/30 ACRYLAMIDE/DADMAC; 1600000 MW); FD&C BLUE NO. 1

Drug Facts

Active ingredient

Benzalkonium Chloride, 0.5%

Purpose

Antiseptic handwash

Uses

- for handwashing to decrease bacteria on the skin

Warnings

For external use only

Do not use

- in eyes

When using the product

- if in eyes, rinse promptly and thoroughly with water
- discontinue use if irritation and redness develop

Stop use and ask a doctor if skin irritation or redness occurs for more than 72 hours

Keep out of reach of children. If swallowed, get medical help or contact a Poison Control Center right away.

Directions

- wet hands and apply product
- scrub hands and forearms
- rinse thoroughly and dry

Other information

- for additional information, see Safety Data Sheet (SDS)
- for emergency medical information in USA call 1.800.328.0026. If located outside the United States, call collect 1.651.222.5352.

INACTIVE INGREDIENT

Inactive ingredients water (aqua), cocamine oxide, hexylene glycol, PEG-180, glycerin, hydroxyethylcellulose, cocamidopropyl PG-dimonium chloride phosphate, phenoxyethanol, myristamide DIPA, myristamine oxide, methyl gluceth-20, glyceryl caprylate/caprate, PEG-12 dimethicone, potassium citrate, blue 1, polyquatemium-7

Questions? call 1.800.392.3392

Principal display panel and representative label

ECOLAB

EcoCare™ 280

Hand Cleaner/Sanitizer

Active Ingredient:

Benzalkonium

chloride 0.5%

1250 mL (42.3 US FL OZ)

This product may be patented

www.ecolab.com/patents

Ecolab · 1 Ecolab Place · St. Paul MN 55102 USA ·

tel: 1 800 392 3392

© 2022 Ecolab USA Inc. · All rights reserved | Todos los derechos reservados

Made in U.S.A. | Hecho en EE.UU.

www.ecolab.com · 778784/5300/0122